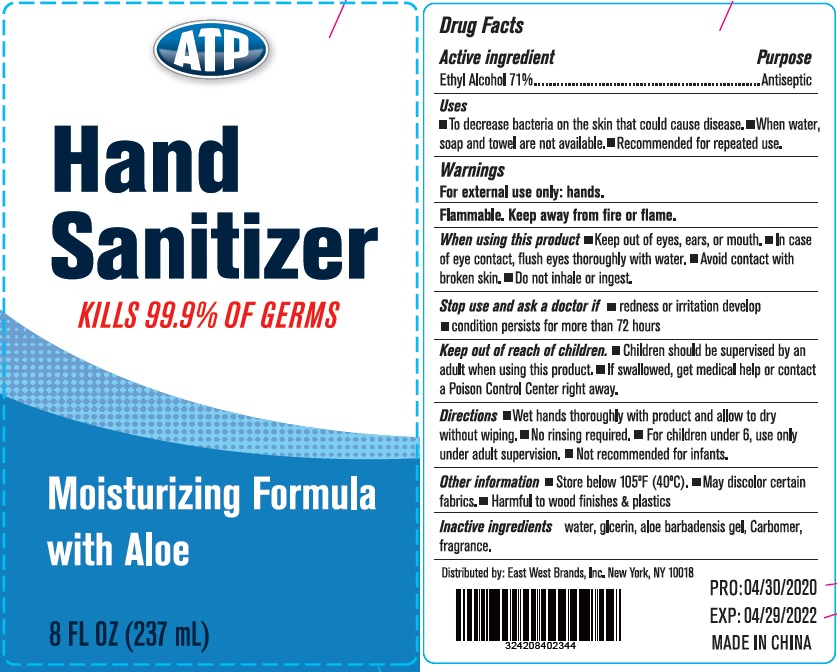 DRUG LABEL: ATP Hand Sanitizer Moisturizing Formula with Aloe
NDC: 75780-009 | Form: GEL
Manufacturer: NINGBO MEINEKE Biotech Technology Co., Ltd.
Category: otc | Type: HUMAN OTC DRUG LABEL
Date: 20200525

ACTIVE INGREDIENTS: alcohol 71 mL/100 mL
INACTIVE INGREDIENTS: WATER; PROPYLENE GLYCOL; ALOE VERA LEAF; GLYCERIN; TROLAMINE

Drug facts

Active ingredient(s) Purpose

Ethyl Alcohol 71% ............... Antiseptic

PURPOSE

- To decrease bacteria on the skin that could cause disease.
- When water, soap and towel are not available.
- Recommendd for repeated use.

KEEP OUT OF REACH OF CHILDREN

- Children should be supervised by an adult when using this product.
- If swallowed, get medical help or contact a Poison Control Center right away.

INDICATIONS AND USAGE

- Wet hands thoroughly with product and allow to dry without wiping
- No rinsing required
- For Children under 6, use only under adult supervision
- No recommended for infants.

WARNINGS

For external use only: hands
Flammable. Keep away from fire or flame.

When using this product

- Keep out of eyes, ears, or mouth
- In case of eye contact, flush eyes thoroughly with water
- Avoid contact with broken skin
- Do not inhale or ingest

Stop use and ask a doctor if

- redness or irritation develop
- condition persists for more than 72 hours

Other information:

- Store below 105℉(40℃)
- May discolor certain fabrics
- Harmful to wood finishes and plastics

INACTIVE INGREDIENT

Water, Glycerin, Aloe Barbadensis gel, carbomer, fragrance